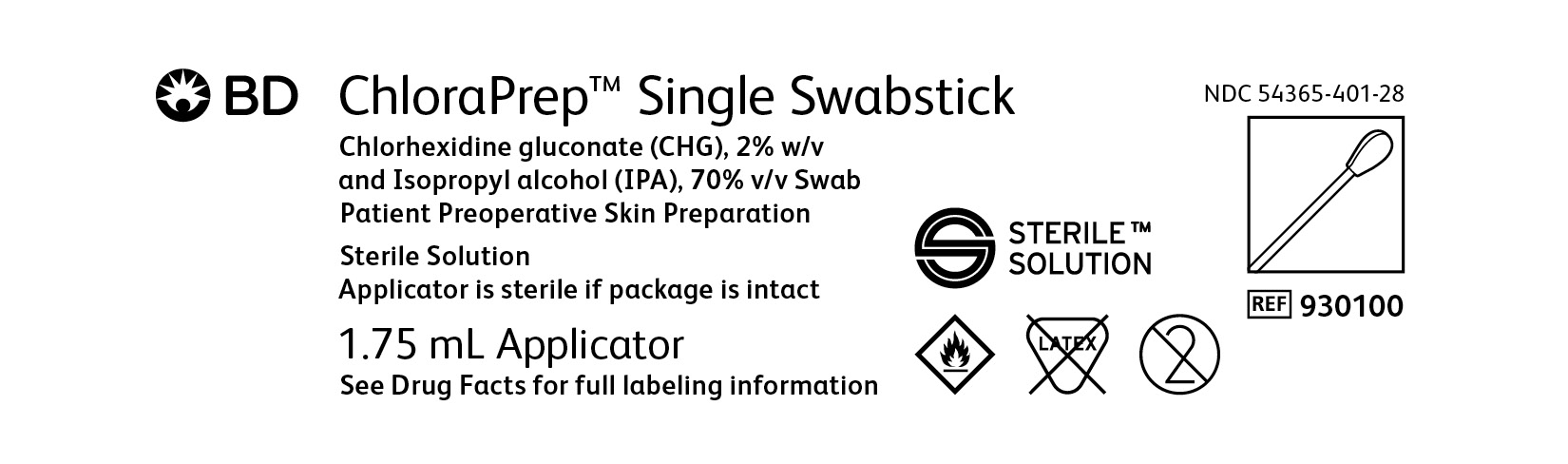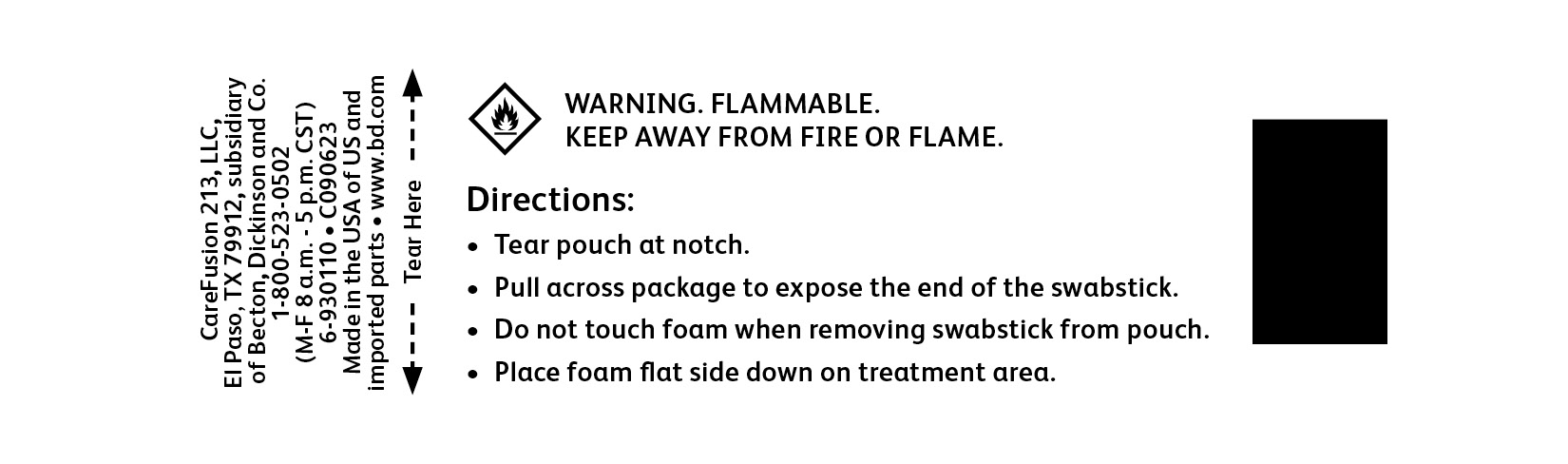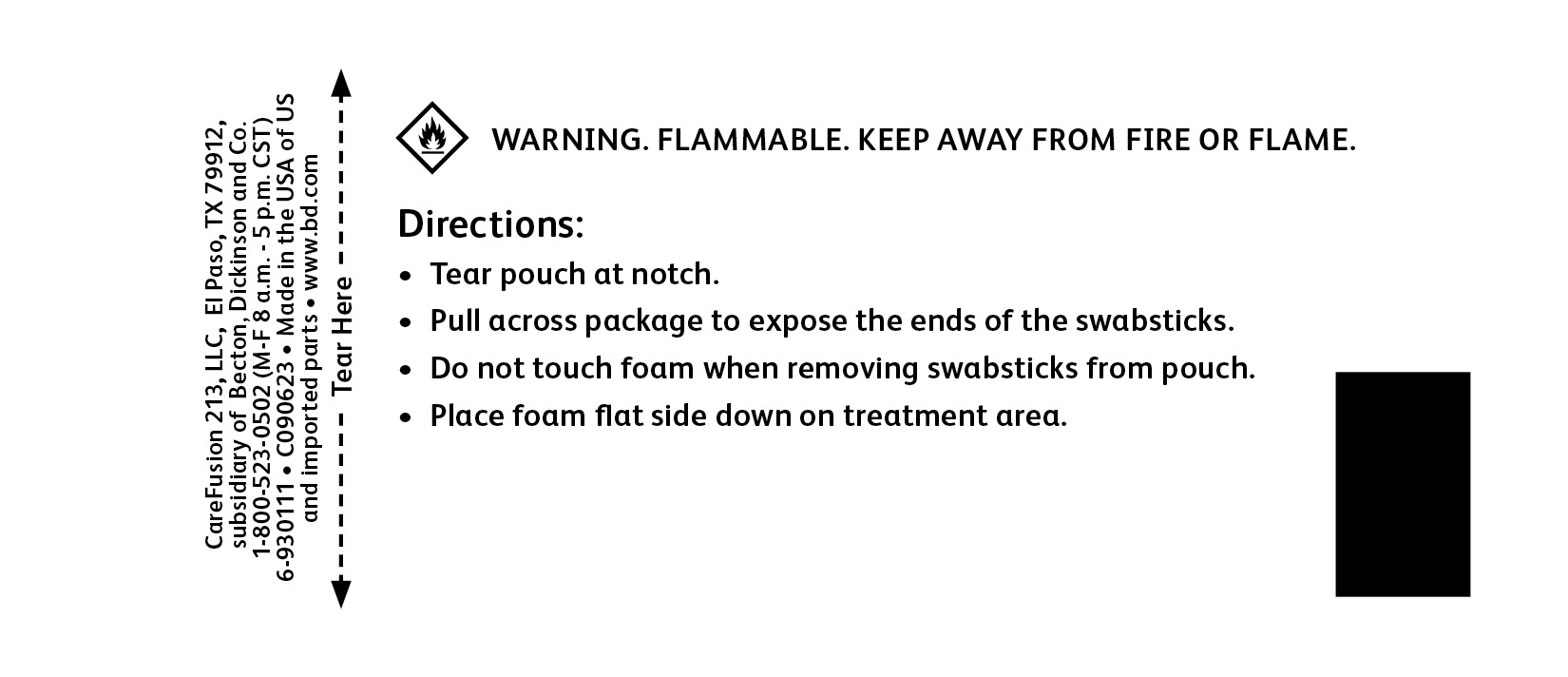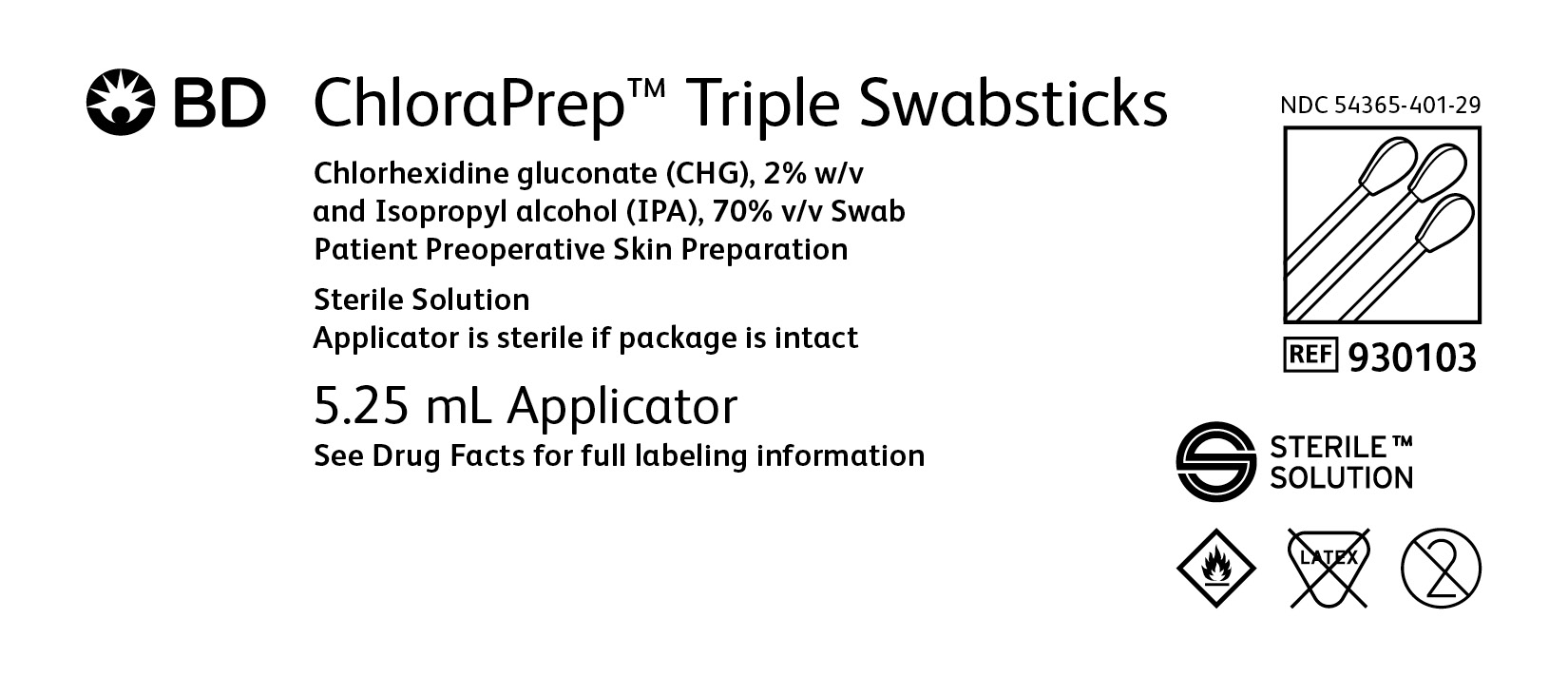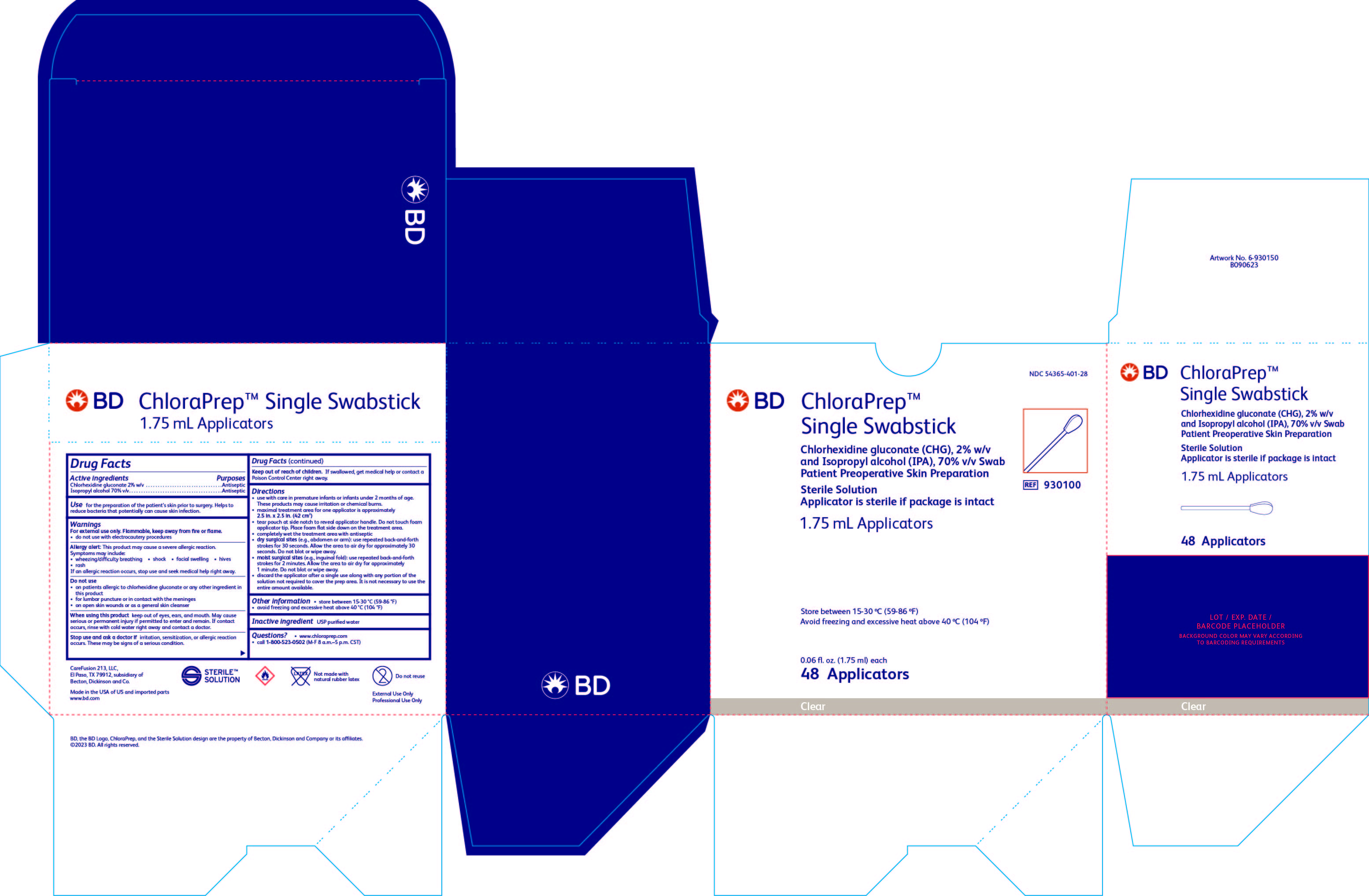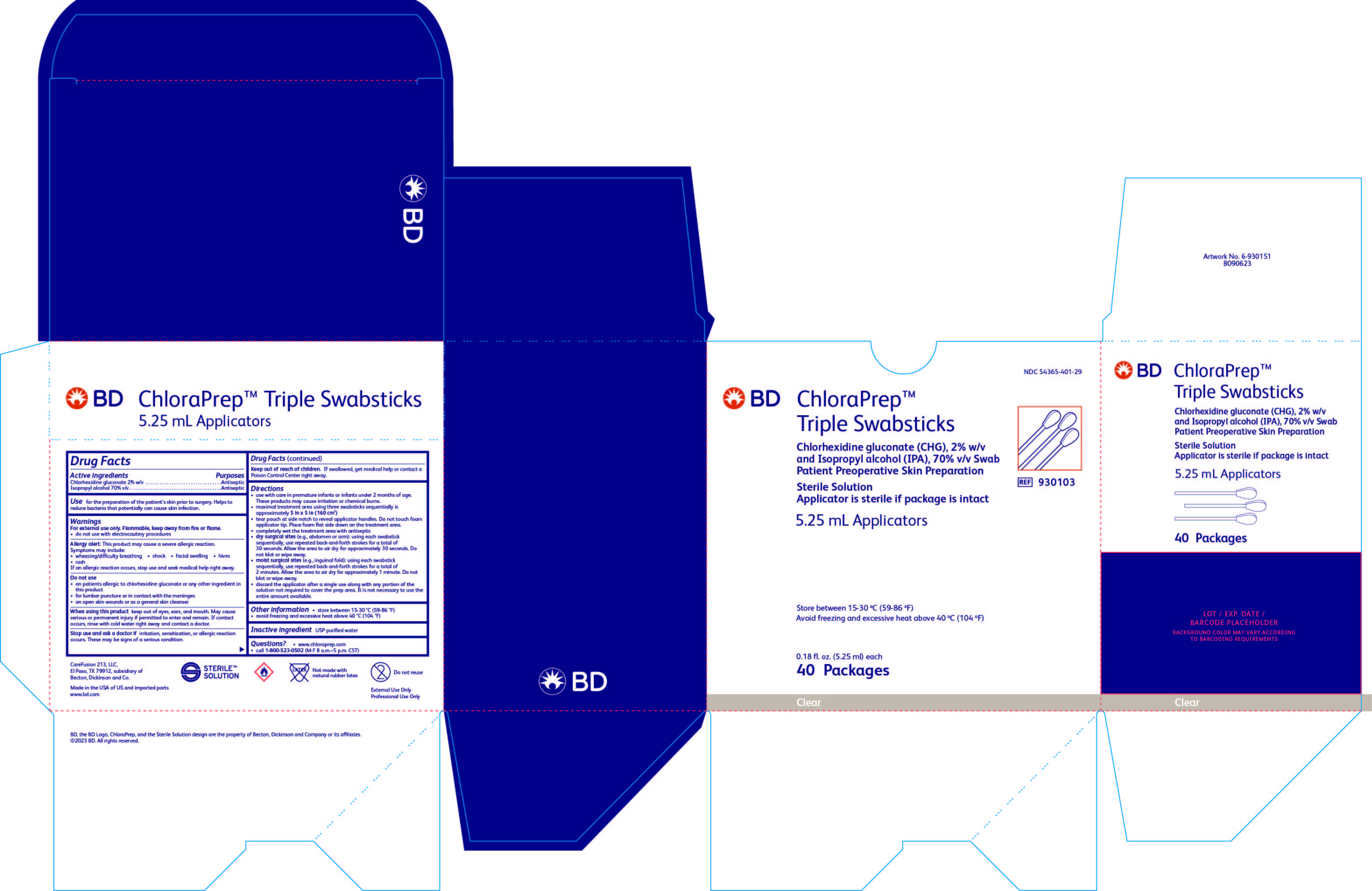 DRUG LABEL: ChloraPrep Swabstick
NDC: 54365-401 | Form: SOLUTION
Manufacturer: CareFusion 213 LLC
Category: otc | Type: HUMAN OTC DRUG LABEL
Date: 20251017

ACTIVE INGREDIENTS: CHLORHEXIDINE GLUCONATE 20 mg/1 mL; ISOPROPYL ALCOHOL 0.7 mL/1 mL
INACTIVE INGREDIENTS: WATER

BD ChloraPrep™ Swabsticks

BD ChloraPrep™ Single Swabstick 1.75 mL Applicators Active ingredients

Chlorhexidine gluconate (CHG), 2% w/v

and Isopropyl alcohol (IPA), 70% v/v

Purpose

Antiseptic

Use

for the preparation of the patient's skin prior to surgery. Helps to reduce bacteria that potentially can cause skin infection.

Warnings

For external use only. Flammable, keep away from fire or flame.

- do not use with electrocautery procedures

Allergy alert:

This product may cause a severe allergic reaction.

Symptoms may include:

- wheezing/difficulty breathing
- shock
- facial swelling
- hives
- rash

If an allergic reaction occurs, stop use and seek medical help right away.

Do not use

- on patients allergic to chlorhexidine gluconate or any other ingredient in this product
- for lumbar puncture or in contact with the meninges
- on open skin wounds or as a general skin cleanser

When using this product

keep out of eyes, ears, and mouth. May cause serious or permanent injury if permitted to enter and remain. If contact occurs, rinse with cold water right away and contact a doctor.

Stop use and ask a doctor if

irritation, sensitization, or allergic reaction occurs. These may be signs of a serious condition.

Keep out of reach of children.

If swallowed, get medical help or contact a Poison Control Center right away.

Directions

- use with care in premature infants or infants under 2 months of age. These products may cause irritation or chemical burns.
- maximal treatment area for one applicator
- one single swabstick applicator is approximately 2.5 in. x 2.5 in. (42 cm^2)
- tear pouch at side notch to reveal applicator handles. Do not touch foam applicator tip. Place foam flat side down on the treatment area.
- completely wet the treatment area with antiseptic
- dry surgical sites (e.g., abdomen or arm): use repeated back-and-forth strokes for 30 seconds. (When using the triple swabstick applicators, use each swabstick sequentially within the 30 seconds). Allow the area to air dry for approximately 30 seconds. Do not blot or wipe away.
- moist surgical sites (e.g., inguinal fold): use repeated back-and-forth strokes for 2 minutes. (When using the triple swabstick applicators, use each swabstick sequentially within the 2 minutes). Allow the area to air dry for approximately 1 minute. Do not blot or wipe away.
- discard the applicator after a single use along with any portion of the solution not required to cover the prep area. It is not necessary to use the entire amount available.

Other information

- store between 15-30 ºC (59-86 °F)
- avoid freezing and excessive heat above 40 ºC (104 °F)

Inactive ingredient

- USP purified water

Questions?

- www.chloraprep.com
- call 1-800-523-0502 (M-F 8 a.m.-5 p.m. CST)

BD ChloraPrep™ Triple Swabstick 5.25 mL Applicators Active ingredients

Chlorhexidine gluconate 2% w/v

Isopropyl alcohol 70% v/v

Purposes

Antiseptic

Antiseptic

Use

for the preparation of the patient's skin prior to surgery. Helps to reduce bacteria that potentially can cause skin infection.

Warnings

For external use only. Flammable, keep away from fire or flame.

- do not use with electrocautery procedures

Allergy alert

This product may cause a severe allergic reaction.

Symptoms may include:

- wheezing/difficulty breathing
- shock
- facial swelling
- hives
- rash

If an allergic reaction occurs, stop use and seek medical help right away.

Do not use

- on patients allergic to chlorhexidine gluconate or any other ingredient in this product
- for lumbar puncture or in contact with the meninges
- on open skin wounds or as a general skin cleanser

When using this product

keep out of eyes, ears, and mouth. May cause serious or permanent inury if permitted to enter and remain. If contact occurs, rinse with cold water right away and contact a doctor.

Stop use and ask a doctor if

irritation, sensitization, or allergic reaction occurs. These may be signs of a serious condition.

Keep out of reach of children.

If swallowed, get medical help or contact a Poison Control Center right away.

Directions

- use with care in premature infants or infants under 2 months of age. These products may cause irritation or chemical burns.
- maximal treatment area using three swabsticks sequentially is approximately 5 in. x 5 in. (160 cm^2)
- tear pouch at side notch to reveal applicator handles. Do not touch foam applicator tip. Place foam flat side down on the treatment area.
- completely wet the treatment area with antiseptic
- dry surgical sites (e.g., abdomen or arm): using each swabstick sequentially, use repeated back-and-forth strokes for a total of 30 seconds. Allow the area to air dry for approximately 30 seconds. Do not blot or wipe away.
- moist surgical sites (e.g., inguinal fold): using each swabstick sequentially, use repeated back-and-forth strokes for a total of 2 minutes. Allow the area to air dry for approximately 1 minute. Do not blot or wipe away.
- discard the applicator after a single use along with any portion of the solution not required to cover the prep area. It is not necessary to use the entire amount available.

Other information

- store between 15-30 ºC (59-86 °F)
- avoid freezing and excessive heat above 40 ºC (104 °F)

Inactive ingredient

USP purified water

Questions?

- www.chloraprep.com
- call 1-800-523-0502 (M-F 8 a.m.-5 p.m. CST)

BD ChloraPrep™ Single Swabstick Package/Label Principal Display Panel

PRINCIPAL DISPLAY PANEL-CARTON

BD ChloraPrep™ Single Swabstick

Chlorhexidine gluconate (CHG), 2% w/v

and Isopropyl alcohol (IPA), 70% v/v Swab

Patient Preoperative Skin Preparation

Sterile Solution

Applicator is sterile if package is intact

1.75 mL Applicators

NDC 054365-401-28

Ref 930100

BD ChloraPrep™ Triple Swabsticks

Chlorhexidine gluconate (CHG), 2% w/v and Isopropyl alcohol (IPA), 70% v/v Swab

Patient Preoperative Skin Preparation

Sterile Solution

Applicator is sterile if package is intact

5.25 mL Applicators

NDC 54365-401-29

REF 930103